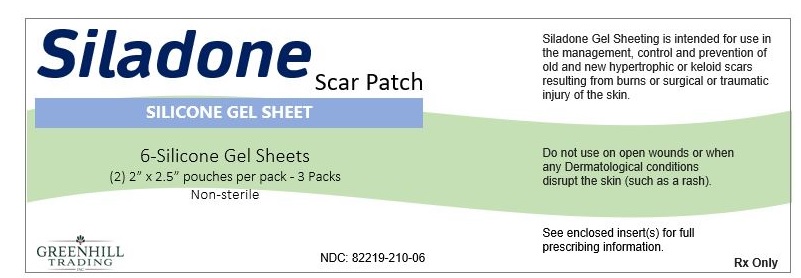 DRUG LABEL: Siladone Scar Patch
NDC: 82219-210
Manufacturer: Greenhill Trading, Inc.
Category: other | Type: MEDICAL DEVICE
Date: 20220302

Siladone Scar Patch

INDICATIONS
Gel Sheeting is intended for use in the management, control, and prevention of old and new hypertrophic or keloid scars resulting from burns or surgical or traumatic injury of the skin.

CONTRAINDICATIONS
Do not use on open wounds or when any Dermatological conditions disrupt the skin (such as a rash).

HOW SUPPLIED
Non-sterile product is labeled as such and supplied in a protective package within a protective outer container.

WARNINGS, PRECAUTIONS, ADVERSE REACTIONS
Possible complications include:

- Superficial maceration of the skin

- Rash,

- Skin Discoloration

- Pruritus,

- Sheeting tack and thickness vary

Rashes have been observed on skin under the gel sheeting, this has been attributed to poor or insufficient hygiene. Similar rashes have been attributed to gel sheeting being wrapped too tightly. Should a rash occur, stop using the gel sheeting for 12 hours followed by using the gel sheeting for 12 hours. If the rash persists, a physician should be contacted, and gel sheeting use should be discontinued.

Discoloration of the skin covered by silicone gel sheeting has been reported, particularly in dark skinned patients. This effect appears to be transient and may be similar to the discoloration experienced whenever an area of skin is covered for extended periods of time.

Some patients report differences in gel sheeting surface tack and thickness from sheet to sheet. Perception of tack is subjective and the adhesive characteristic of gel sheeting may vary. These variations do not affect the function of the product.

Small bubbles may form after repeated washing and use. This does not have an impact on the function of the product.

Do not use creams, lotions, sun block or other silicone products on your skin when wearing silicone gel sheeting. These products will create a barrier between the scar site and silicone gel, preventing a proper healing environment.

For children under 5 years of age, use under adult supervision.

INSTRUCTIONS FOR USE
Silicone Gel Sheeting

1. Wash both scar and hands per cleaning instructions.
2. Open the non-sterile pouch containing the Silicone Gel Sheet.
3. Clear gel sheeting is covered on both sides by a plastic film. Fabric gel sheeting is covered on the tacky side by a plastic film. Remove plastic film prior to use.
4. The gel sheet may be cut into smaller pieces using scissors or a scalpel. Once you have determined the appropriate size of sheeting to use, apply tacky side to the scar. The gel sheeting should fully cover the scar and extend ¼ inch all the way around the scar border.
5. The exposed surface of the gel sheeting may be covered with surgical tape or bandage to help hold in place and to prevent sticking to other surfaces.
6. If the product is worn during sleep, it should be secured. Use of medical tape (Epi-Tape) or other means is recommended to keep the product from falling off.

CLEANING INSTRUCTIONS

Remove the gel sheet every 12 hours to wash both the scar and the gel sheet. In a basin of warm water, work up a small amount of lather with the soap. Gently wash the piece of gel sheeting in the soapy water, rinse, and then air dry. Make sure the sheeting is completely dry before re-applying to the scar. After washing, rinsing, and drying the scar site re-apply the piece of gel sheeting.

WEARING TIME

Optimal wearing time for silicone gel sheeting is 24 hours per day.
If it is not possible to wear the gel sheet for the recommended 24-hour period, a minimum of 12 hours per day is required, washing per the instructions above once in that period. Follow this procedure each day, washing and re-applying the gel sheeting to the scar for 1 to 2 weeks. At that time the piece of gel sheeting will begin to lose its adhesive quality and/or may become embedded with surface dirt. When this occurs, discard the piece of gel sheeting, and apply a new piece.

The overall optimal period of use is usually 8 to 12 weeks.

Incident Notice: Any serious incident that has occurred in relation to this product should be reported to and the competent authority of the Member State in which the user and/or patient is established.

Product Label

NDC: 82219-210-06

Rx Only

Siladone Scar Patch

SILICONE GEL SHEET

6-Silicone Gel Sheets
(2) 2" X 2.5" pouches per pack - 3 packs
Non-sterile
GREENHILL
TRADING

Siladone Gel Sheeting is intended for use in the management, control and prevention of old and new hypertrophic or keloid scars resulting from burns or surgical or traumatic injury of the skin.

Do not use on open wounds or when any Dermatological conditions disrupt the skin (such as a rash).

See enclosed insert(s) for full
prescribing information.